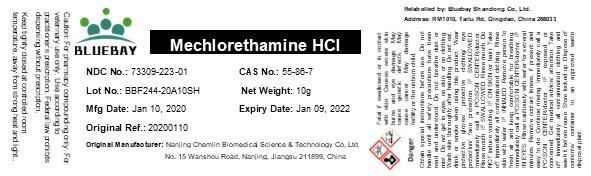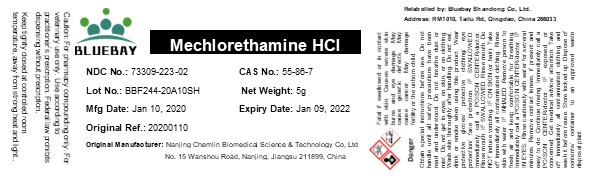 DRUG LABEL: Mechlorethamine HCl
NDC: 73309-223 | Form: POWDER
Manufacturer: BLUEBAY SHANDONG CO.,LTD
Category: other | Type: BULK INGREDIENT
Date: 20201223

ACTIVE INGREDIENTS: MECHLORETHAMINE HYDROCHLORIDE 1 g/1 g

Mechlorethamine HCl